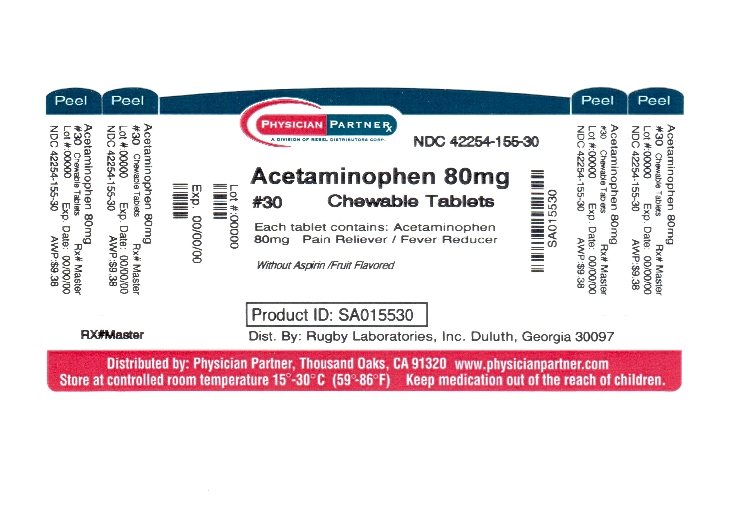 DRUG LABEL: Acetaminophen
NDC: 42254-155 | Form: TABLET, CHEWABLE
Manufacturer: Rebel Distributors Corp
Category: otc | Type: HUMAN OTC DRUG LABEL
Date: 20120216

ACTIVE INGREDIENTS: ACETAMINOPHEN 80 mg/1 1
INACTIVE INGREDIENTS: ASPARTAME; SUCROSE; D&C RED NO. 27; FD&C YELLOW NO. 6; MAGNESIUM STEARATE; CELLULOSE, MICROCRYSTALLINE; STEARIC ACID

Acetaminophen Drug Facts

Active ingredient

Acetaminophen

Purpose

Pain Reliever / Fever Reducer

Keep Out of Reach of Children

In case of overdose, get medical help or contact a Poison Control Center right away. Prompt medical attention is critical, even if you do not notice any signs or symptoms.

Uses

temporarily reduces fever and relieves minor aches and pains caused by

headache
common cold
flu
toothache
sore throat

Warnings

Liver warning: This product contains acetaminophen. Severe liver damage may occur if the child takes

more than 5 doses in 24 hours, which is the maximum daily amount

with other drugs containing acetaminophen

Sore throat warning: If sore throat is severe, lasts for more than 2 days or is accompanied or fillowed by fever, headache, rash, nausea or vomiting, consult a doctor promptly.

Do not use with any other drug containing acetaminophen (prescription or nonprescription). If you are not sure whether a drug contains acetaminophen, ask a doctor or pharmacist.

Ask a doctor before use if the child has liver disease

Ask a doctor or pharmacist before use if the child is taking the blood thinning drug warfarin.

Stop use and ask a doctor if

pain gets worse or lasts more than 5 days

fever gets worse or lasts more than 3 days

redness or swelling is present

any new symptoms appear

Directions

this product does not contain directions or complete warnings for adult use

find correct does on chart below

if possible, use weight to dose, otherwise use age

chew tablets before swallowing

give dose every 4 hours while symptoms last

do not give more than 5 doses in 24 hours

Weight (pounds) | Age (years) | Dose (tablets)
72 - 95 | 11 - 12 | 4 - 6
60 - 71 | 9 - 10 | 4 - 5
48 - 59 | 6 - 8 | 4
36 - 47 | 4 - 5 | 3
24 - 35 | 2 - 3 | 2
under 24 | under 2 | ask a doctor